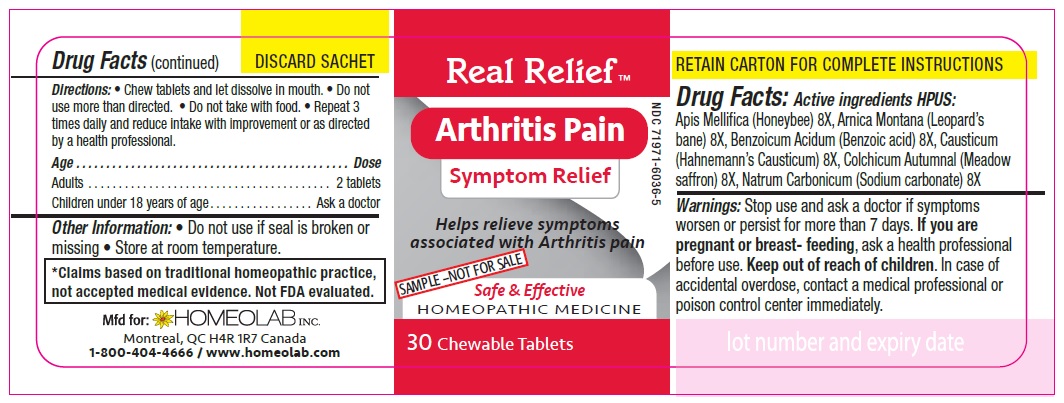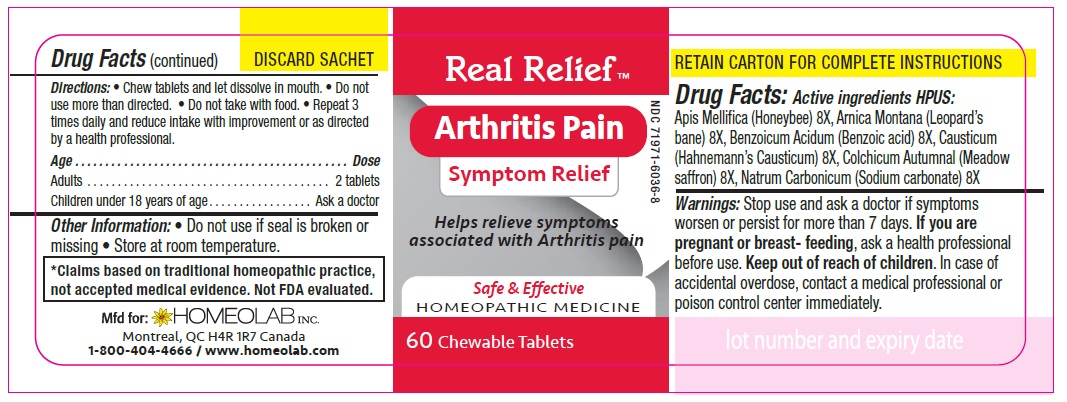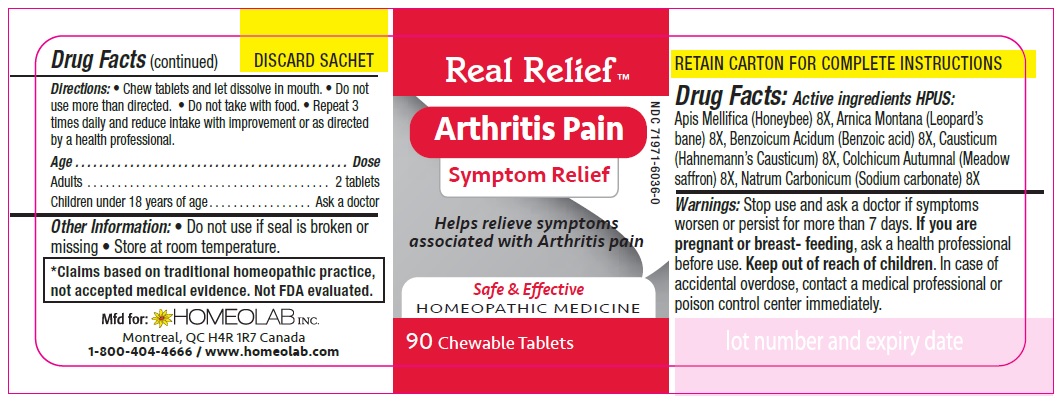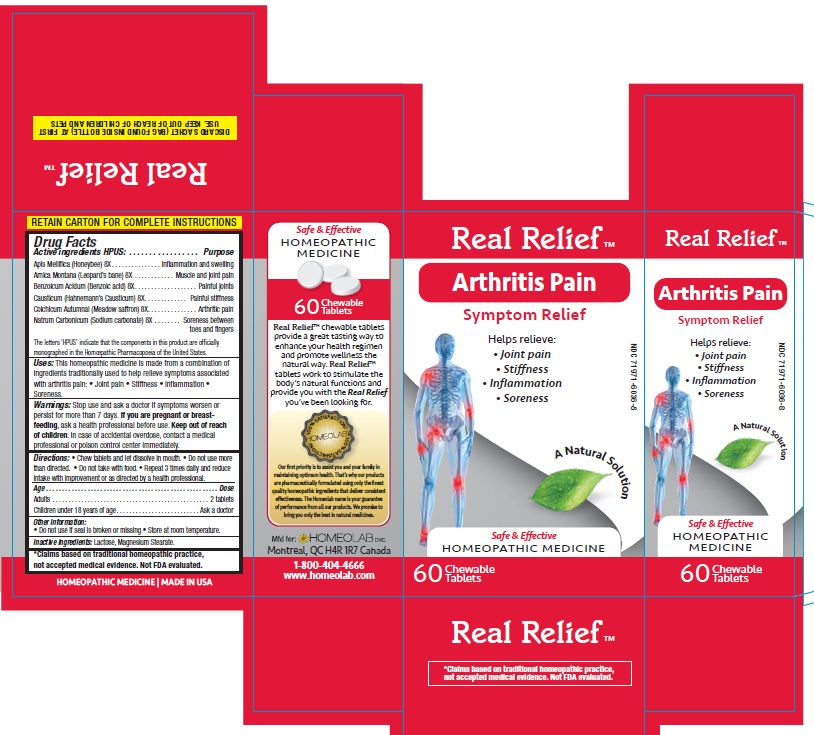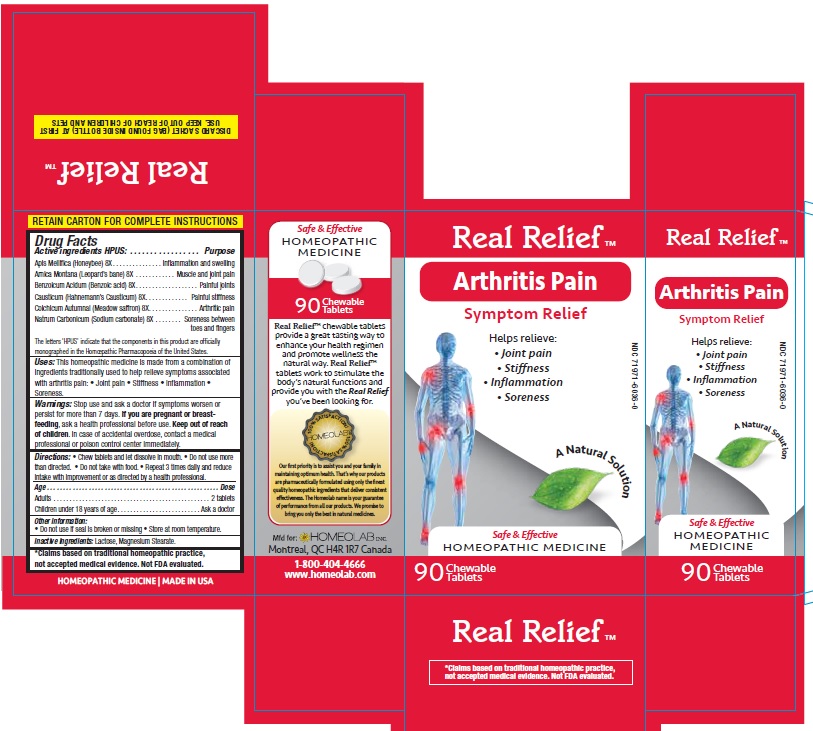 DRUG LABEL: Real Relief
NDC: 65808-324 | Form: TABLET
Manufacturer: GMP Laboratories of America, Inc.
Category: homeopathic | Type: HUMAN OTC DRUG LABEL
Date: 20201229

ACTIVE INGREDIENTS: APIS MELLIFERA 8 [hp_X]/1 1; ARNICA MONTANA 8 [hp_X]/1 1; BENZOIC ACID 8 [hp_X]/1 1; CAUSTICUM 8 [hp_X]/1 1; COLCHICUM AUTUMNALE BULB 8 [hp_X]/1 1; SODIUM CARBONATE 8 [hp_X]/1 1
INACTIVE INGREDIENTS: LACTOSE MONOHYDRATE; MAGNESIUM STEARATE

Active Ingredients HPUS:

Apis Mellifica (Honeybee) 8 [hp-X]

Arnica Montana (Leopard’s bane) 8 [hp-X]

Benzoicum Acidum (Benzoic acid) 8 [hp-X]

Causticum (Hahnemann’s Causticum) 8 [hp-X]

Colchicum Autumnale (Meadow saffron) 8 [hp-X]

Natrum Carbonicum (Sodium carbonate) 8 [hp-X]

Purpose

Homeopathic remedy helps relieve symptoms of all types of arthritis pain:

- painful stiffness
- arthritic pain
- painful joints
- inflammation and swelling
- muscle and joint pain
- soreness between toes and fingers

The letters 'HPUS' indicate that the components in this product are officially monographed in the Homoeopathic Pharmacopoeia of the United States.

*Claims based on traditional homeopathic practice, not accepted medical evidence. Not FDA evaluated.

Uses

This homeopathic medicine is made from a combination of ingredients traditionally used to help relieve symptoms associated

- with arthritis
- joint pain
- stiffness
- inflammation
- soreness

Warnings

Stop use and ask a doctor if symptoms worsen or last for more than 7 days.

If you are pregnant or breastfeeding, ask a health professional before use.

Keep out of reach of children.

In case of accidental overdose, contact a medical professional or poison control center immediately.

Directions

Chew tablets and let dissolve in mouth.

Do not use more than directed.

Do not take with food.

Repeat 3 times daily and reduce intake with improvement or as directed by a health professional

Age…………………………………………………………........ Dose

Adults and Children 12 years of age and older………...... 2 tablets

Children 2 to 11 years of age…...……………………............ 1 tablet

Children under 2 years of age……………………................. Ask a doctor

Other information

- Store at room temperature.
- Do not use if seal is broken or missing.

Inactive ingredients

Lactose, Magnesium Stearate.